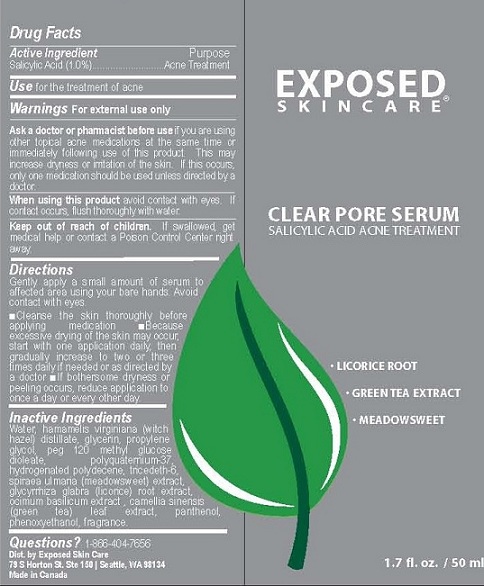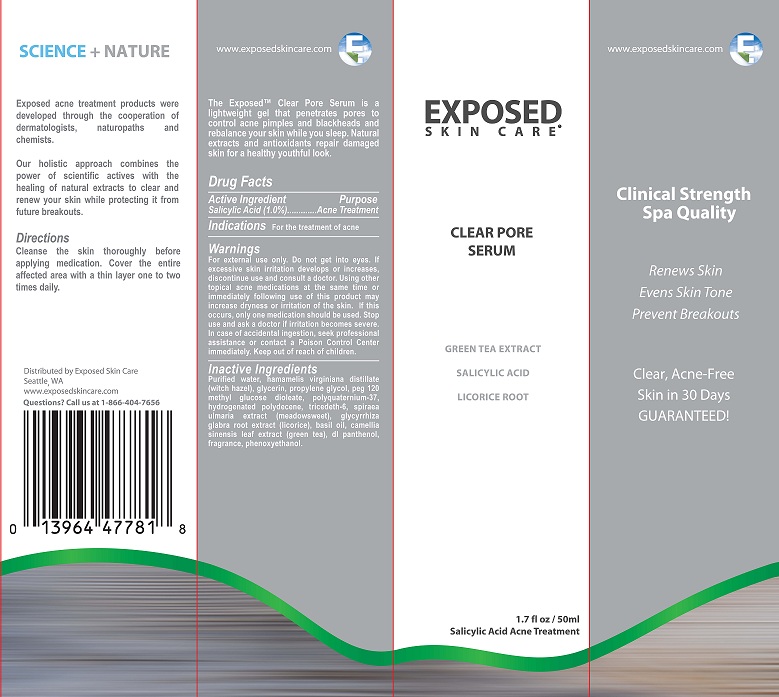 DRUG LABEL: CLEAR PORE SERUM
NDC: 55878-103 | Form: GEL
Manufacturer: Halogent, LLC (DBA Exposed Skin Care) 
Category: otc | Type: HUMAN OTC DRUG LABEL
Date: 20130313

ACTIVE INGREDIENTS: SALICYLIC ACID 1 g/100 mL
INACTIVE INGREDIENTS: WATER; HAMAMELIS VIRGINIANA ROOT BARK/STEM BARK; GLYCERIN; PROPYLENE GLYCOL; PEG-120 METHYL GLUCOSE DIOLEATE; POLYQUATERNIUM-37 (10000 MPA.S); HYDROGENATED POLYDECENE (550 MW); TRIDECETH-6; FILIPENDULA ULMARIA FLOWER; LICORICE; OCIMUM BASILICUM FLOWERING TOP; CAMELLIA SINENSIS WHOLE; PANTHENOL; PHENOXYETHANOL

PURPOSE

ACNE TREATMENT

ACTIVE INGREDIENT

SALICYLIC ACID (1.0%)

USE

FOR THE TREATMENT OF ACNE

WARNINGS FOR EXTERNAL USE ONLY

Ask a doctor or pharmacist before use if you are using other topical acne medications at the same time or immediately following use of this product. This may increase dryness or irritation of the skin. If this occurs, only one medication should be used unless directed by a doctor

When using this product avoid contact with eyes. If contact occurs, flush thoroughly with water.

Directions

Gently apply a small amount of serum to affected area using your bare hands. Avoid contact with eyes.

- Cleanse the skin thoroughly before applying medication
- Because excessive drying of the skin may occur, start with one application daily, then gradually increase to two or three times daily if needed or as directed by a doctor
- If bothersome dryness or peeling occurs, reduce application to once a day or every other day.

Inactive Ingredients

Water, hamamelis virginiana (witch hazel) distillate, glycerin, propylene glycol, peg 120 methyl glucose dioleate, polyquaternium-37, hydrogenated polydecene, tricedeth-6, spiraea ulmaria (meadowsweet) extract, glycyrrhiza glabra (licorice) root extract, ocimum basilicum extract , camellia sinensis (green tea) leaf extract, panthenol, phenoxyethanol, fragrance.

KEEP OUT OF REACH OF CHILDREN, IF SWALLOWED, GET MEDICAL HELP OR CONTACT A POISON CONTROL CENTER RIGHT AWAY.

Questions? 1-866-404-7656